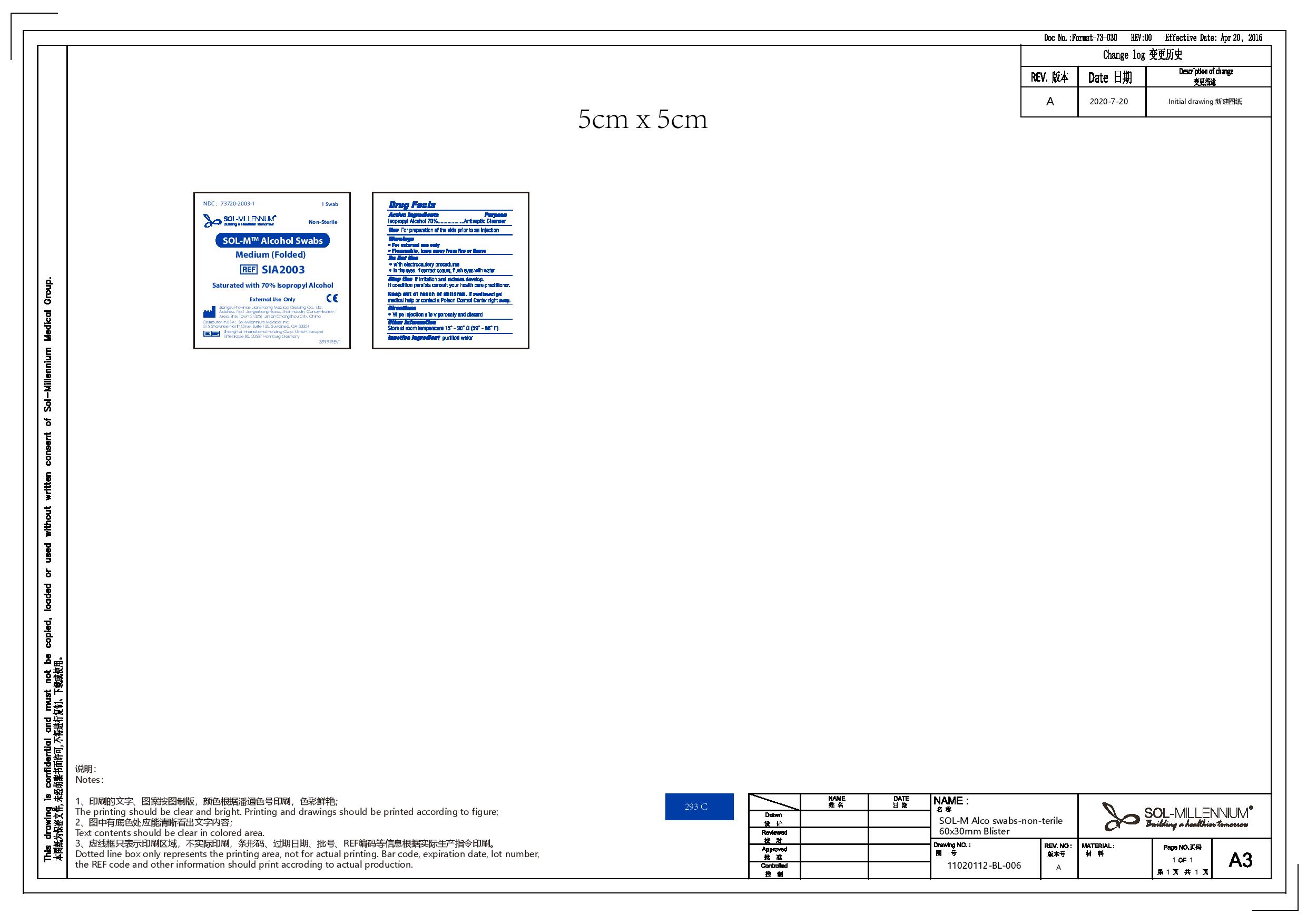 DRUG LABEL: Sol-M Alcohol Swabs Medium (folded) non sterile
NDC: 73720-2003 | Form: SWAB
Manufacturer: Sol-Millennium Medical Inc
Category: otc | Type: HUMAN OTC DRUG LABEL
Date: 20220622

ACTIVE INGREDIENTS: ALCOHOL 0.7 mL/1 mL
INACTIVE INGREDIENTS: WATER

Sol-M Alcohol Swabs Medium (folded) non sterile

Active Ingredients

Isopropyl Alcohol 70%

Purpose

Isopropyl Alcohol 70%................Antiseptic Cleanser

Uses

For preparation of the skin prior to an injection

Warnings

For external use only

Flammable, keep away from fire or flame

Do not use

- with electrocautery procedures
- In the eyes. If contact occurs, flush eyes with water

Stop use if

If irritation and redness develop. If conditions persists consult your healthcare practicioner.

Keep out of reach of children. If swallowed get medical help or contact a Poison Control Center right away.

Directions

Wipe injection site vigorously and discard

Other Information

Store at room temperature 15 - 30 C (59 - 86 F)

Inactive Ingredients

purified water